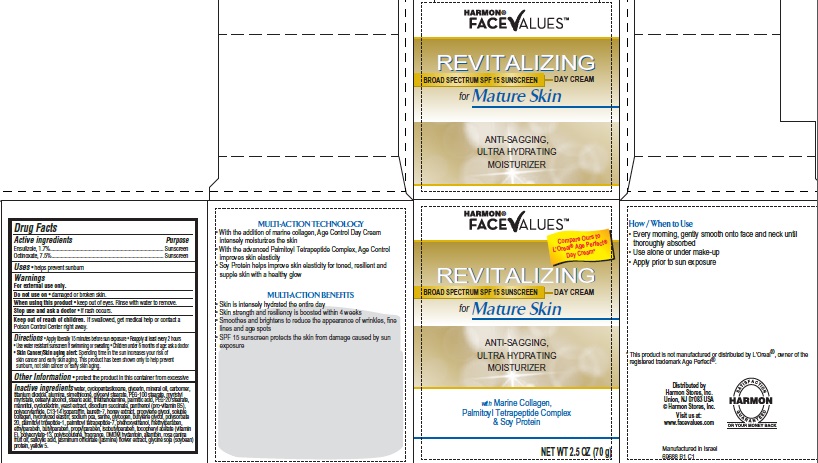 DRUG LABEL: Harmon Face Values Revitalizing Age Control Anti-Sagging Ultra Hydrating Day SPF 15
NDC: 63940-688 | Form: CREAM
Manufacturer: Harmon Stores Inc.
Category: otc | Type: HUMAN OTC DRUG LABEL
Date: 20140923

ACTIVE INGREDIENTS: ENSULIZOLE 1.7 g/100 g; OCTINOXATE 7.5 g/100 g
INACTIVE INGREDIENTS: WATER; CYCLOMETHICONE 5; GLYCERIN; MINERAL OIL; TITANIUM DIOXIDE; ALUMINUM OXIDE; DIMETHICONE; SILICON DIOXIDE; GLYCERYL MONOSTEARATE; PEG-100 STEARATE; MYRISTYL MYRISTATE; CETOSTEARYL ALCOHOL; STEARIC ACID; TROLAMINE; PALMITIC ACID; PEG-20 STEARATE; MANNITOL; YEAST; SODIUM SUCCINATE ANHYDROUS; PANTHENOL; C13-14 ISOPARAFFIN; LAURETH-7; HONEY; PROPYLENE GLYCOL; MARINE COLLAGEN, SOLUBLE; HYDROLYZED ELASTIN, BOVINE, ALKALINE (1000 MW); SODIUM PYRROLIDONE CARBOXYLATE; SERINE; GLYCOGEN; BUTYLENE GLYCOL; POLYSORBATE 20; PALMITOYL TETRAPEPTIDE-7; PHENOXYETHANOL; METHYLPARABEN; ETHYLPARABEN; BUTYLPARABEN; PROPYLPARABEN; ISOBUTYLPARABEN; .ALPHA.-TOCOPHEROL ACETATE; DMDM HYDANTOIN; ALLANTOIN; ROSA CANINA FRUIT OIL; SALICYLIC ACID; JASMINUM OFFICINALE FLOWER; SOY PROTEIN; FD&C YELLOW NO. 5

Harmon® FaceValues™ Revitalizing Broad Spectrum SPF 15 Sunscreen Day Cream for Mature Skin

Active ingredients

Ensulizole, 1.7%

Octinoxate, 7.5%

Purpose

Sunscreen

Uses

- helps prevent sunburn

Warnings

For external use only.

Do not use on

- damaged or broken skin.

When using this product

- keep out of eyes. Rinse with water to remove.

Stop use and ask a doctor

- if rash occurs.

Keep Out of Reach of Children.

If swallowed, get medical help or contact a Poison Control Center right away.

Directions

- Apply liberally 15 minutes before sun exposure
- Reapply at least every 2 hours
- Use water resistant sunscreen if swimming or sweating
- Children under 6 months of age: ask a doctor
- Skin Cancer/Skin aging alert: Spending time in the sun increases your risk of skin cancer and early skin aging. This product has been shown only to help prevent sunburn, not skin cancer or early skin aging.

Other Information

- protect the product in this container from excessive

Inactive ingredients

water, cyclopentasiloxane, glycerin, mineral oil, carbomer, titanium dioxide, alumina, simethicone, glyceryl stearate, PEG-100 stearate, myristyl myristate, cetearyl alcohol, stearic acid, triethanolamine, palmitic acid, PEG-20 stearate, mannitol, cyclodextrin, yeast extract, disodium succinate, panthenol (pro-vitamin B5), polyacrylamide, C13-14 isoparaffin, laureth-7, honey extract, propylene glycol, soluble collagen, hydrolyzed elastin, sodium pca, serine, glycogen, butylene glycol, polysorbate 20, palmitoyl tripeptide-1, palmitoyl tetrapeptide-7, phenoxyethanol, methylparaben, ethylparaben, butylparaben, propylparaben, isobutylparaben, tocopheryl acetate (vitamin E), polyacrylate-13, polyisobutene, fragrance, DMDM hydantoin, allantoin, rosa canina fruit oil, salicylic acid, jasminum officinale (jasmine) flower extract, glycine soja (soybean) protein, yellow 5.

Principal Display Panel

Harmon®
FACEVALUES™

Compare Ours to L’Oreal® Age Perfect® Day Cream*

REVITALIZING
BROAD SPECTRUM SPF 15 SUNSCREEN DAY CREAM
for Mature Skin

ANTI-SAGGING,
ULTRA HYDRATING
MOISTURIZER

with Marine Collagen,
Palmitoyl Tetrapeptide Complex
& Soy Protein

Net Wt 2.5 OZ (70 g)

MULTI-ACTION TECHNOLOGY

- With the addition of marine collagen, Age Control Day Cream intensely moisturizes the skin
- With the advanced Palmitoyl Tetrapeptide Complex, Age Control improves skin elasticity
- Soy Protein helps improve skin elasticity for toned, resilient and supple skin with a healthy glow

MULTI-ACTION BENEFITS

- Skin is intensely hydrated the entire day
- Skin strength and resiliency is boosted within 4 weeks
- Smoothes and brightens to reduce the appearance of wrinkles, fine lines and age spots
- SPF 15 sunscreen protects the skin from damage caused by sun exposure

How/When to Use

- Every morning, gently smooth onto face and neck until thoroughly absorbed
- Use alone or under make-up
- Apply prior to sun exposure

*This product is not manufactured or distributed by L’Oreal®, owner of the registered trademark Age Perfect®.

Distributed by
Harmon Stores, Inc.
Union, NJ 07083 USA
© Harmon Stores, Inc.

Visit us at:
www.facevalues.com

SATISFACTION
GUARANTEED
OR YOUR MONEY BACK

Manufactured in Israel
69688 B1 C1

Carton Label